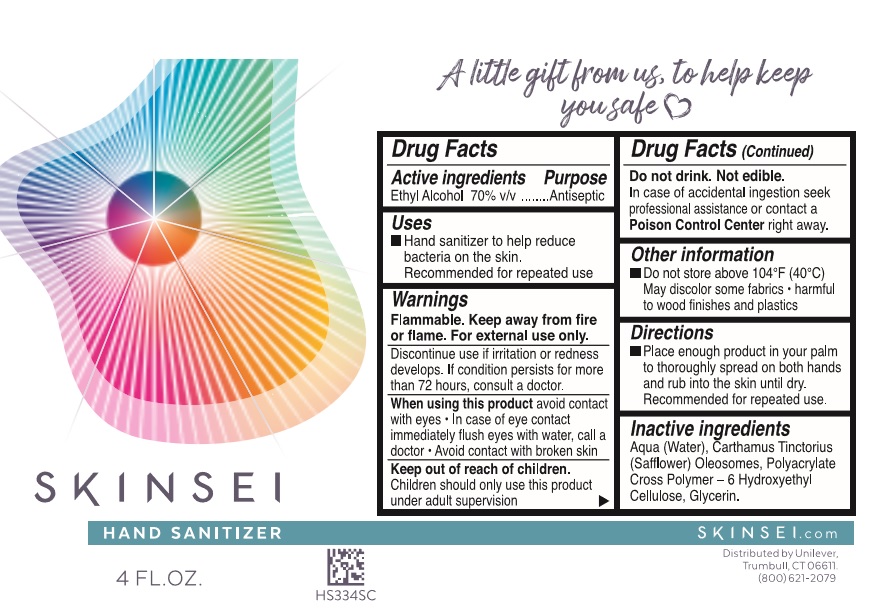 DRUG LABEL: SKINSEI
NDC: 64942-1740 | Form: LIQUID
Manufacturer: Conopco Inc. d/b/a/ Unilever
Category: otc | Type: HUMAN OTC DRUG LABEL
Date: 20241107

ACTIVE INGREDIENTS: ALCOHOL 700 mg/1 mL
INACTIVE INGREDIENTS: WATER; GLYCERIN; CARTHAMUS TINCTORIUS SEED OLEOSOMES

Skinsei Hand Sanitizer

SKINSEI HAND SANITIZER - Alcohol liquid

Skinsei Hand Sanitizer

Drug Facts

Active ingredient

Ethyl Alcohol 70%

Purpose

Antiseptic

Uses

Hand sanitizer to help reduce bacteria on the skin. Recommended for repeated use

Warnings

Flammable. Keep away from fire or flame
For external use only
Discontinue use if irritation or redness develops. If condition persists for more than 72 hours, consult a doctor.
When using this product avoid contact with eyes · In case of contact, flush eyes with water, call a doctor · Avoid contact with broken skin

Do not drink. Not edible.
In case of accidental ingeston seek professional assistance or contact a Poison Contro Center right away.

Keep out of reach of children.
Children should only use this product under adult supervision

Directions

• Place enough product in your palm to thoroughly spread on both hands and rub into the skin until dry. Recommended for repeated use.

Other information

• Do not store above 104˚F (40˚C). May discolor some fabrics · harmful to wood finishes and plastics

Inactive ingredients

Aqua (Water), Carthamus Tinctorius (Safflower) Oleosomes, Polyacrylate Cross Polymer - 6 Hydroxyethyl Cellulose, Glycerin.

QUESTIONS

(800) 621-2079.